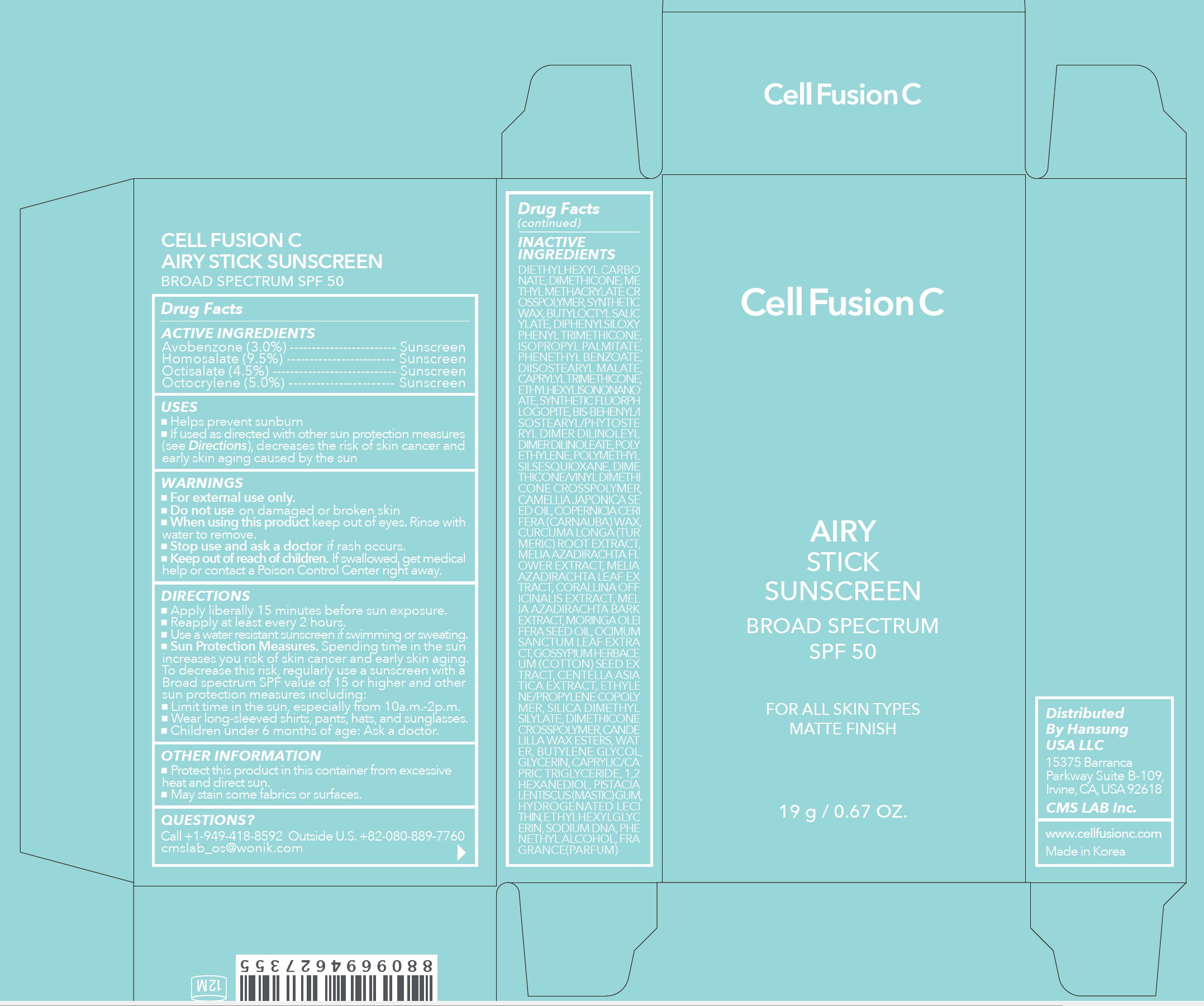 DRUG LABEL: Cell Fusion C Airy Stick Sunscreen Broad Spectrum SPF 50
NDC: 52554-9071 | Form: STICK
Manufacturer: CMS LAB Inc.
Category: otc | Type: HUMAN OTC DRUG LABEL
Date: 20250214

ACTIVE INGREDIENTS: HOMOSALATE 9.5 g/100 g; OCTOCRYLENE 5 g/100 g; OCTISALATE 4.5 g/100 g; AVOBENZONE 3 g/100 g
INACTIVE INGREDIENTS: WATER

52554-9071-1 Cell Fusion C Airy Stick Sunscreen Broad Spectrum SPF 50 19g

Drug Facts

ACTIVE INGREDIENTS

Avobenzone 3.0%
Homosalate 9.5%
Octisalate 4.5%
Octocrylene 5.0%

PURPOSE

Sunscreen

USES

- Helps prevent sunburn
- If used as directed with other sun protection measures (see Directions), decreases the risk of skin cancer and early skin aging caused by the sun

WARNINGS

For external use only

- Do not use on damaged or broken skin

- When using this product keep out of the eyes. Rinse with water to remove.

- Stop use and ask a doctor if rash occurs

- Keep out of reach of children. If swallowed, get medical help or contact a Poison Control Center right away.

DIRECTIONS

- Apply liberally 15 minutes before sun exposure.
- Reapply at least every 2 hours.
- Use a water resistant sunscreen if swimming or sweating.
- Sun Protection Measures. Spending time in the sun increases your risk of skin cancer and early skin aging. To decrease this risk, regularly use a sunscreen with a Broad Spectrum SPF value of 15 or higher and other sun protection measures including:

- Limit time in the sun, especially from 10 a.m.-2 p.m.
- Wear long-sleeved shirts, pants, hats, and sunglasses
- Children under 6 months of age: Ask a doctor.

OTHER INFORMATION

- Protect this product in this container from excessive heat and direct sun.
- May stain some fabrics or surfaces.

INACTIVE INGREDIENTS

Diethylhexyl Carbonate, Dimethicone, Methyl Methacrylate Crosspolymer, Synthetic Wax, Butyloctyl Salicylate, Diphenylsiloxy Phenyl Trimethicone, Isopropyl Palmitate, Phenethyl Benzoate, Diisostearyl Malate, Caprylyl Trimethicone, Ethylhexyl Isononanoate, Synthetic Fluorphlogopite, Bis-Behenyl/Isostearyl/Phytosteryl Dimer Dilinoleyl Dimer Dilinoleate, Polyethylene, Polymethylsilsesquioxane, Dimethicone/Vinyl Dimethicone Crosspolymer, Camellia Japonica Seed Oil, Copernicia Cerifera (Carnauba) Wax, Curcuma Longa (Turmeric) Root Extract, Melia Azadirachta Flower Extract, Melia Azadirachta Leaf Extract, Corallina Officinalis Extract, Melia Azadirachta Bark Extract, Moringa Oleifera Seed Oil, Ocimum Sanctum Leaf Extract, Gossypium Herbaceum (Cotton) Seed Extract, Centella Asiatica Extract, Ethylene/Propylene Copolymer, Silica Dimethyl Silylate, Dimethicone Crosspolymer, Candelilla Wax Esters, Water, Butylene Glycol, Glycerin, Caprylic/Capric Triglyceride, 1,2-Hexanediol, Pistacia Lentiscus (Mastic) Gum, Hydrogenated Lecithin, Ethylhexylglycerin, Sodium DNA, Phenethyl Alcohol, Fragrance (Parfum)

QUESTIONS?

Call +1-949-418-8592
Outside U.S. +82-080-889-7760
cmslab_os@wonik.com

Distributed By
Hansung USA LLC
15375 Barranca Parkway
Suite B-109, Irvine, CA USA 92618
CMS LAB Inc.
www.cellfusionc.com
Made in Korea

PRINCIPAL DISPLAY PANEL: 19 g / 0.67 OZ. Carton

Cell Fusion C

AIRY
STICK
SUNSCREEN
BROAD SPECTRUM
SPF 50
FOR ALL SKIN TYPES
MATTE FINISH
19 g / 0.67 OZ.